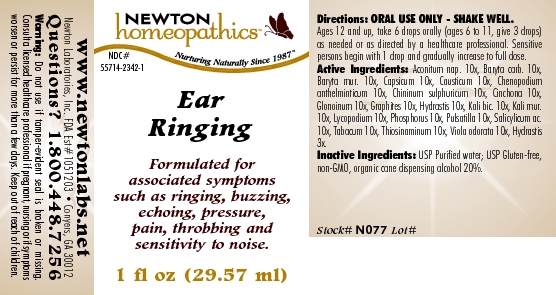 DRUG LABEL: Ear Ringing 
NDC: 55714-2342 | Form: LIQUID
Manufacturer: Newton Laboratories, Inc.
Category: homeopathic | Type: HUMAN OTC DRUG LABEL
Date: 20110301

ACTIVE INGREDIENTS: Aconitum Napellus 10 [hp_X]/1 mL; Barium Carbonate 10 [hp_X]/1 mL; Barium Chloride Dihydrate 10 [hp_X]/1 mL; Capsicum 10 [hp_X]/1 mL; Causticum 10 [hp_X]/1 mL; Dysphania Ambrosioides 10 [hp_X]/1 mL; Quinine Sulfate 10 [hp_X]/1 mL; Cinchona Officinalis Bark 10 [hp_X]/1 mL; Nitroglycerin 10 [hp_X]/1 mL; Graphite 10 [hp_X]/1 mL; Goldenseal 10 [hp_X]/1 mL; Potassium Dichromate 10 [hp_X]/1 mL; Potassium Chloride 10 [hp_X]/1 mL; Lycopodium Clavatum Spore 10 [hp_X]/1 mL; Phosphorus 10 [hp_X]/1 mL; Pulsatilla Vulgaris 10 [hp_X]/1 mL; Salicylic Acid 10 [hp_X]/1 mL; Tobacco Leaf 10 [hp_X]/1 mL; Allylthiourea 10 [hp_X]/1 mL; Viola Odorata 10 [hp_X]/1 mL; Goldenseal 3 [hp_X]/1 mL
INACTIVE INGREDIENTS: Alcohol

Ear Ringing

INDICATIONS & USAGE SECTION

Ear Ringing Formulated for associated symptoms such as ringing, buzzing, echoing, pressure, pain, throbbing and sensitivity to noise.

DOSAGE & ADMINISTRATION SECTION

Directions: ORAL USE ONLY - SHAKE WELL. Ages 12 and up, take 6 drops orally (ages 6 to 11, give 3 drops) as needed or as directed by a healthcare professional. Sensitive persons begin with 1 drop and gradually increase to full dose.

OTC - ACTIVE INGREDIENT SECTION

Aconitum nap. 10x, Baryta carb. 10x, Baryta mur. 10x, Capsicum 10x, Causticum 10x, Chenopodium anthelminticum 10x, Chininum sulphuricum 10x, Cinchona 10x, Glonoinum 10x, Graphites 10x, Hydrastis 10x, Kali bic. 10x, Kali mur.10x, Lycopodium 10x, Phosphorus 10x, Pulsatilla 10x, Salicylicum ac.10x, Tabacum 10x, Thiosinaminum 10x, Viola odorata 10x, Hydrastis 3x.

OTC - PURPOSE SECTION

Formulated for associated symptoms such as ringing, buzzing, echoing, pressure, pain, throbbing and sensitivity to noise.

INACTIVE INGREDIENT SECTION

Inactive Ingredients: USP Purified Water; USP Gluten-free, non-GMO, organic cane dispensing alcohol 20%

QUESTIONS SECTION

www.newtonlabs.net Newton Laboratories, Inc. FDA Est # 1051203 - Conyers, GA 30012
Questions? 1.800.448.7256

WARNINGS SECTION

Warning: Do not use if tamper - evident seal is broken or missing. Consult a licensed healthcare professional if pregnant, nursing or if symptoms worsen or persist for more than a few days. Keep out of reach of children

OTC - PREGNANCY OR BREAST FEEDING SECTION

Consult a licensed healthcare professional if pregnant, nursing or if symptoms worsen or persist for more than a few days.

OTC - KEEP OUT OF REACH OF CHILDREN SECTION

Keep out of reach of children.